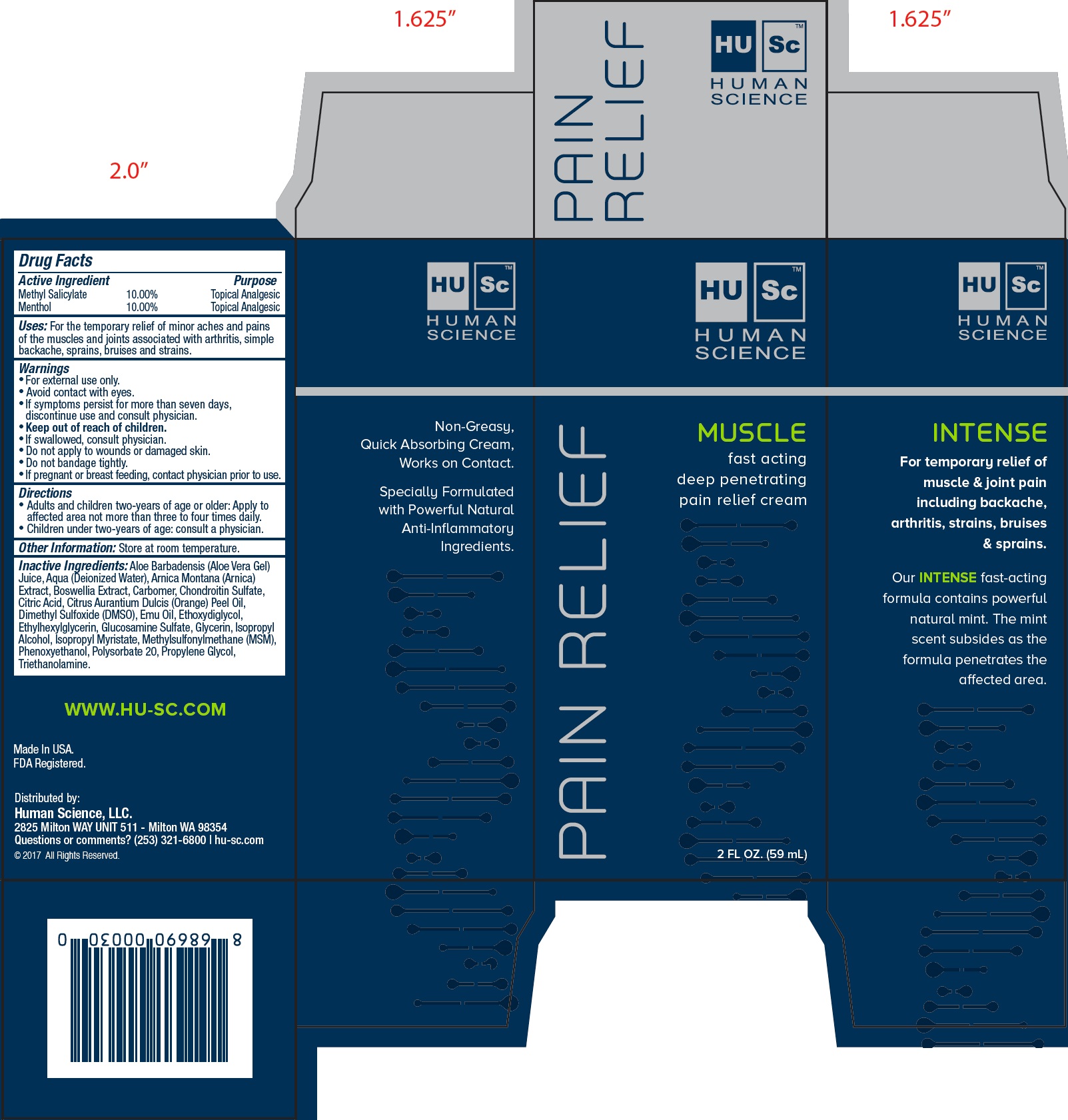 DRUG LABEL: Human Science Muscle Pain Relief
NDC: 71356-818 | Form: CREAM
Manufacturer: Human Science, LLC
Category: otc | Type: HUMAN OTC DRUG LABEL
Date: 20231111

ACTIVE INGREDIENTS: METHYL SALICYLATE 100 mg/1 mL; MENTHOL 100 mg/1 mL
INACTIVE INGREDIENTS: ALOE VERA LEAF; WATER; ARNICA MONTANA; CARBOXYPOLYMETHYLENE; CITRIC ACID MONOHYDRATE; ORANGE OIL; DIMETHYL SULFOXIDE; EMU OIL; DIETHYLENE GLYCOL MONOETHYL ETHER; ETHYLHEXYLGLYCERIN; GLUCOSAMINE SULFATE; GLYCERIN; ISOPROPYL ALCOHOL; ISOPROPYL MYRISTATE; DIMETHYL SULFONE; PHENOXYETHANOL; POLYSORBATE 20; PROPYLENE GLYCOL; TROLAMINE

Human Science Muscle Pain Relief

Active Ingredient

Methyl Salicylate 10.00%

Menthol 10.00%

Purpose

Topical Analgesic

Uses:

For the temporary relief of minor aches and pains of the muscles and joints associated with arthritis, simple backache, sprains, bruises and strains.

Warnings

- For external use only.
- Avoid contact with eyes.
- If symptoms persist for more than seven days, discontinue use and consult physician.

Keep out of reach of children.

- If swallowed, consult physician.

Do not apply

- to wounds or damaged skin.
- Do not bandage tightly.

If pregnant or breast feeding,

contact physician prior to use.

Directions

- Adults and children two-years of age or older: Apply to affected area not more than three to four times daily.
- Children under two-years of age: consult a physician.

Other Information:

Store at room temperature.

Inactive Ingredients:

Aloe Barbadensis (Aloe Vera Gel) Juice, Aqua (Deionized Water), Arnica Montana (Arnica) Extract, Boswellia Extract, Carbomer, Chondroitin Sulfate, Citric Acid, Citrus Aurantium Dulcis (Orange) Peel Oil, Dimethyl Sulfoxide (DMSO), Emu Oil, Ethoxydiglycol, Ethylhexylglycerin, Glucosamine Sulfate, Glycerin, Isopropyl Alcohol, Isopropyl Myristate, Methylsulfonylmethane (MSM), Phenoxyethanol, Polysorbate 20, Propylene Glycol, Triethanolamine.